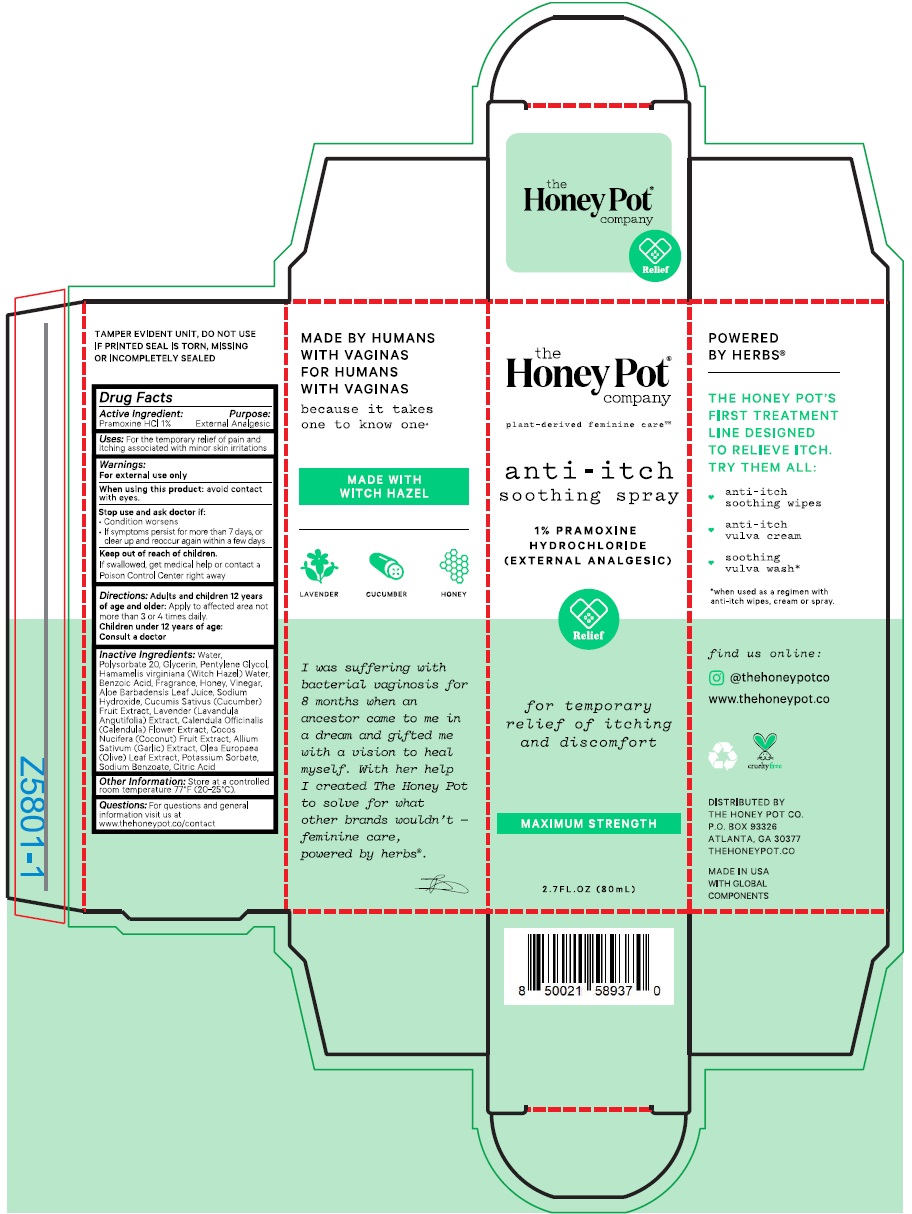 DRUG LABEL: Honey Pot
NDC: 71505-022 | Form: LIQUID
Manufacturer: Disposable Hygiene LLC dba Anthem
Category: otc | Type: HUMAN OTC DRUG LABEL
Date: 20220215

ACTIVE INGREDIENTS: PRAMOXINE HYDROCHLORIDE 10 mg/1 mL
INACTIVE INGREDIENTS: ACETIC ACID; SODIUM HYDROXIDE; LAVENDER OIL; CALENDULA OFFICINALIS FLOWER; GARLIC OIL; OLEA EUROPAEA LEAF; SODIUM BENZOATE; CITRIC ACID MONOHYDRATE; GLYCERIN; PENTYLENE GLYCOL; POLYSORBATE 20; WATER; BENZOIC ACID; ALOE VERA LEAF; WITCH HAZEL; HONEY; CUCUMBER FRUIT OIL; COCONUT OIL; POTASSIUM SORBATE

Disposable Hygiene Anti-itching Cream 80 mL

Active Ingredient(s)

Pramoxine hydrochloride 1% (w/w)

Purpose

External analgesic

Use

For temporary relief of pain and itching associated with minor skin irritations.

Warnings

For external use only.

When using this product: avoid contact with eyes.

Stop use and ask a doctor if: • Condition worsens • If symptoms persist for more than 7 days, or clear up and reoccur again within a few days.

Keep out of reach of children. If swallowed, get medical help or contact a Poison Control Center right away.

Directions

Adults and children 12 years of age and older: Apply to the affected area not more than 3 or 4 times daily. Children under 12 years of age: Consult a doctor

Inactive ingredients

Water, Polysorbate 20, Glycerin, Pentylene Glycol, Hamamelis virginiana (Witch Hazel) Water, Benzoic Acid, Fragrance, Honey, Vinegar, Aloe Barbadensis Leaf Juice, Sodium Hydroxide, Cucumis Sativus (Cucumber) Fruit Extract, Lavender (Lavandula Angustifolia) Extract, Calendula Officinalis (Calendula) Flower Extract, Cocos Nucifera (Coconut) Fruit Extract, Allium Sativum (Garlic) Extract, Olea Europaea (Olive) Leaf Extract, Potassium Sorbate, Sodium Benzoate, Citric Acid

Other information

Store at a controlled room temperature of 77°F (20-25°C).

QUESTIONS

For questions and general information visit us at www.thehoneypot.co/contact

Package Label - Principal Display Panel

80 mL NDC: 71505-022-80